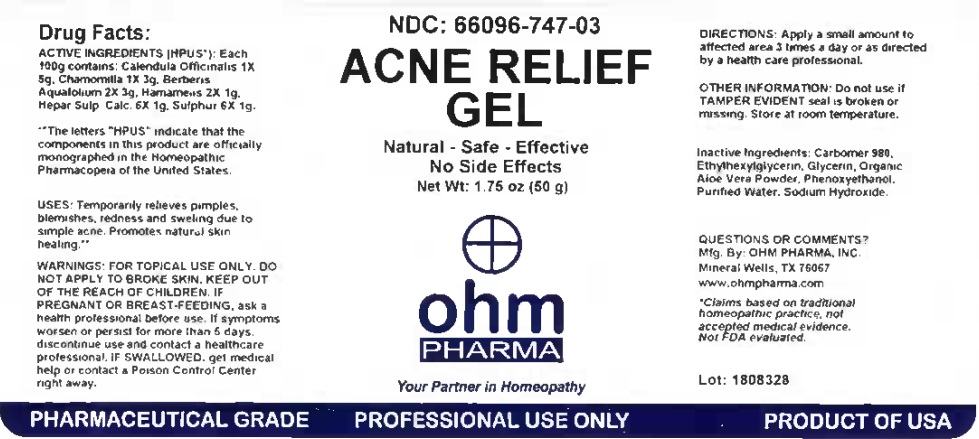 DRUG LABEL: Acne Relief Gel
NDC: 66096-747 | Form: GEL
Manufacturer: OHM PHARMA INC.
Category: homeopathic | Type: HUMAN OTC DRUG LABEL
Date: 20211229

ACTIVE INGREDIENTS: CALENDULA OFFICINALIS FLOWERING TOP 1 [hp_X]/50 g; MATRICARIA CHAMOMILLA 1 [hp_X]/50 g; BERBERIS AQUIFOLIUM ROOT BARK 2 [hp_X]/50 g; HAMAMELIS VIRGINIANA ROOT BARK/STEM BARK 2 [hp_X]/50 g; CALCIUM SULFIDE 6 [hp_X]/50 g; SULFUR 6 [hp_X]/50 g
INACTIVE INGREDIENTS: CARBOMER HOMOPOLYMER TYPE C (ALLYL PENTAERYTHRITOL CROSSLINKED); ETHYLHEXYLGLYCERIN; GLYCERIN; ALOE VERA LEAF; PHENOXYETHANOL; WATER; SODIUM HYDROXYMETHYLGLYCINATE

Acne Relief Gel

Drug Facts:

ACTIVE INGREDIENTS (HPUS*): Each 100g contains: Calendula Officinalis 1X 5g, Chamomilla 1X 3g, Berberis Aquafolium 2X 3g, Hamamelis 2X 1g, Hepar Sulph. Calc. 6X 1g, Sulphur 6X 1g.

**The letters "HPUS" indicate that the components in this product are officially monographed in the Homeopathic Pharmacopeia of the United States.

* Claims based on traditional homeopathic practice, not accepted medical evidence. Not FDA evaluated.

INDICATIONS AND USAGE

USES: Temporarily relieves pimples, blemishes, redness and swelling due to simple acne. Promotes natural skin healing.**

WARNINGS

WARNINGS: FOR TOPICAL USE ONLY. DO NOT APPLY TO BROKE SKIN. KEEP OUT OF REACH OF CHILDREN. IF PREGNANT OR BREAST-FEEDING, ask a health professional before use. If symptoms worsen or persist for more than 5 days, discontinue use and contact a healthcare professional. IF SWALLOWED, get medical help or contact a Poison Control Center right away.

KEEP OUT OF REACH OF CHILDREN

DOSAGE AND ADMINISTRATION

DIRECTIONS: Apply a small amount to affected area 3 times a day or as directed by a health care professional.

OTHER INFORMATION: Do not use if TAMPER EVIDENT seal is broken or missing. Store at room temperature.

INACTIVE INGREDIENT

Inactive ingredients: Carbomer 980, Ethythexyglycerin, Glycerin, Organic Aloe Vera Powder, Phenoxythanol, Purified Water, Sodium Hydroxide.

QUESTIONS OR COMMENTS?

Mfg. By: OHM PHARMA, INC.

Mineral Wells, TX 76067

www.ohmpharma.com

PACKAGE LABEL

NDC: 66096-747-03

ACNE RELIEF GEL

Natural - Safe - Effective

No Side Effects

Net Wt: 1.75 oz (50 g)

ohm

PHARMA

Your Partner in Homeopathy

PURPOSE

Temporay relieves pimples, blemishes, redness and swelling due to simple acne. Promotes natural skin healing. **